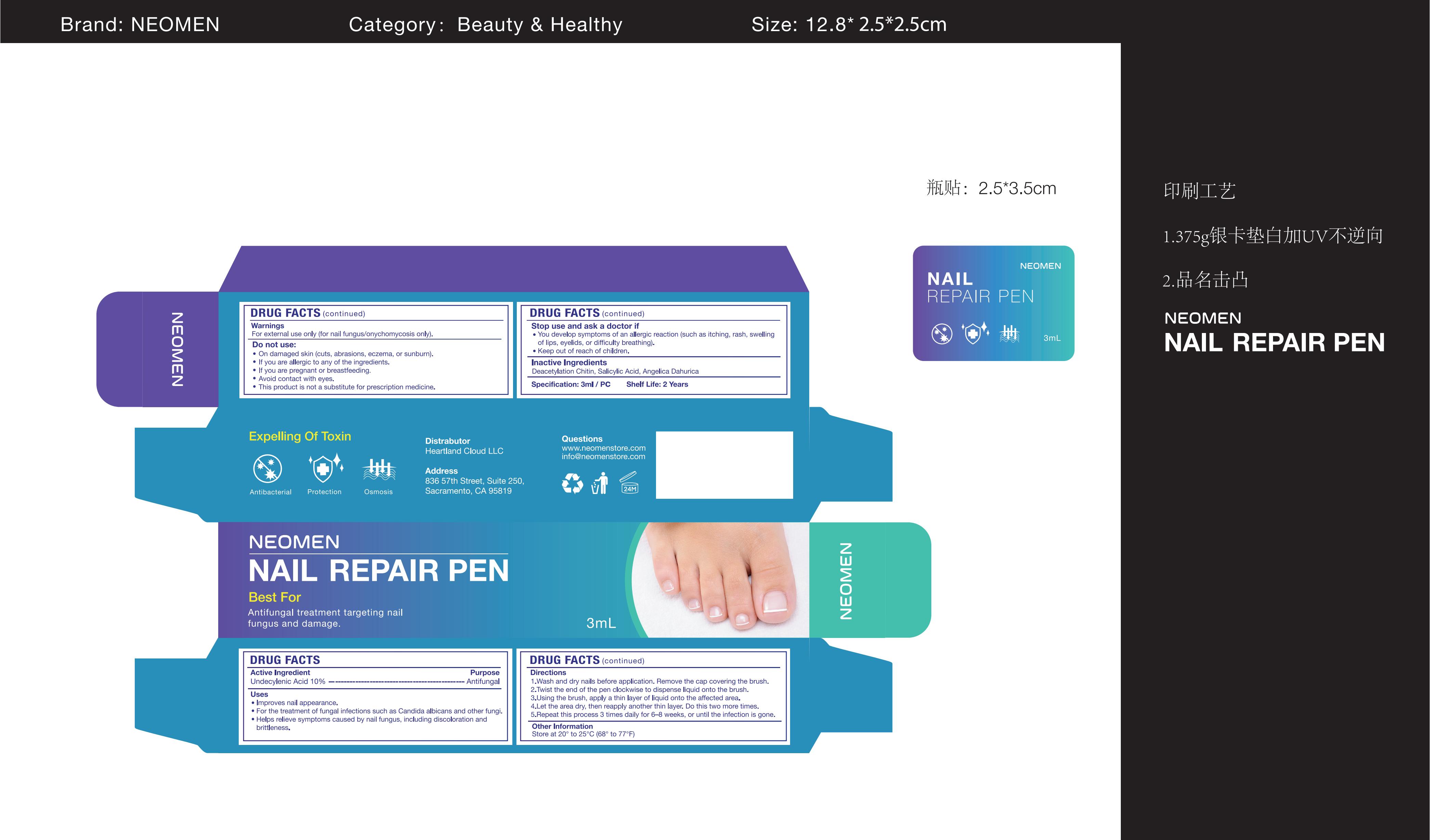 DRUG LABEL: NEOMEN Nail Repair Pen
NDC: 83887-006 | Form: LIQUID
Manufacturer: Changsha Beiliang E-commerce Co., Ltd
Category: otc | Type: HUMAN OTC DRUG LABEL
Date: 20250421

ACTIVE INGREDIENTS: UNDECYLENIC ACID 10 g/100 mL
INACTIVE INGREDIENTS: CHITIN; ANGELICA DAHURICA ROOT; SALICYLIC ACID

83887-006

Active Ingredient

Undecylenic Acid 10%

Purpose

Antifungal

Use

• Improves nail appearance.
• For the treatment of fungal infections such as Candida albicans and other fungi, helps relieve symptoms caused by nail fungus, including discoloration and brittleness.

Warnings

For external use only (for nail fungus/onychomycosis only).
This product is not a substitute for prescription medicine.

Do not use

• On damaged skin (cuts, abrasions, eczema, or sunburn).
• If you are allergic to any of the ingredients.
• If you are pregnant or breastfeeding.

When Using

Avoid contact with eyes.

Stop Use

You develop symptoms of an allergic reaction (such as itching, rash, swelling of lips, eyelids, or difficulty breathing).

Ask Doctor

You develop symptoms of an allergic reaction (such as itching, rash, swelling of lips, eyelids, or difficulty breathing).

Keep Oot Of Reach Of Children

Directions

Wash and dry nails before application. Remove the cap covering the brush.
Twist the end of the pen clockwise to dispense liquid onto the brush.
Using the brush, apply a thin layer of liquid onto the affected area.
Let the area dry, then reapply another thin layer. Do this two more times.
Repeat this process 3 times daily for 6-8 weeks, or until the infection is gone.

Other information

Store at 20° to 25°C (68° to 77°F).

Inactive ingredients

Deacetylation Chitin , Salicylic Acid , Angelica Dahurica Root

Questions

www.neomenstore.com